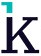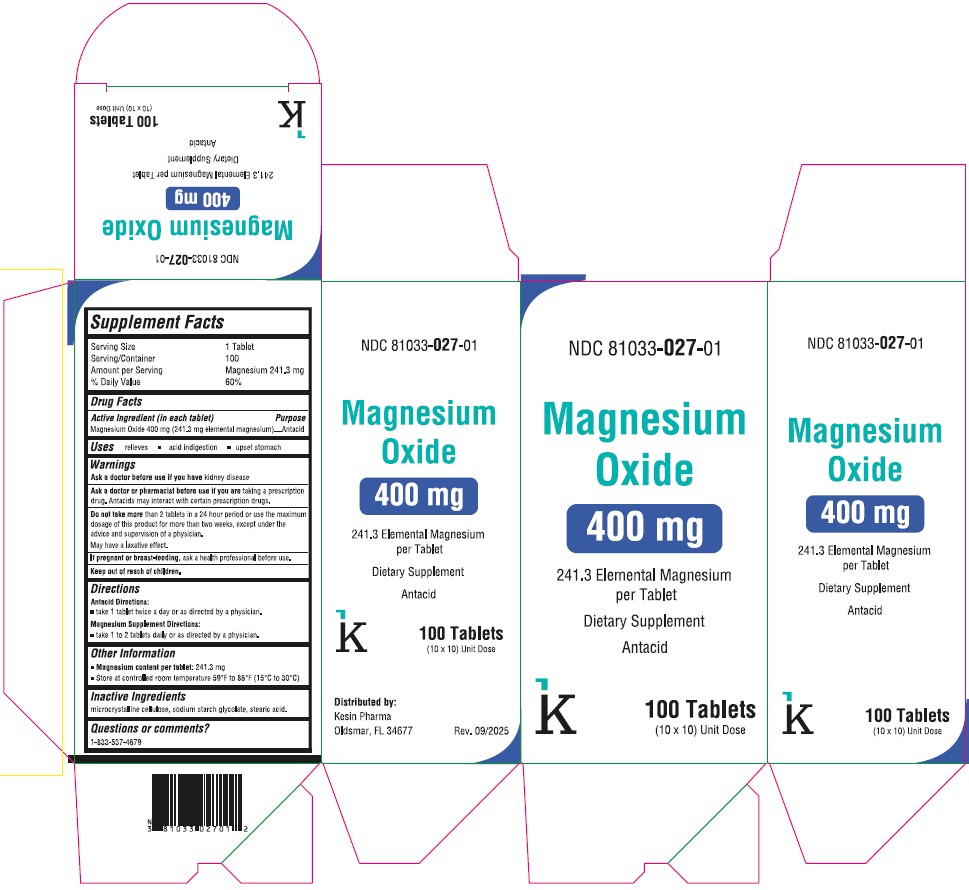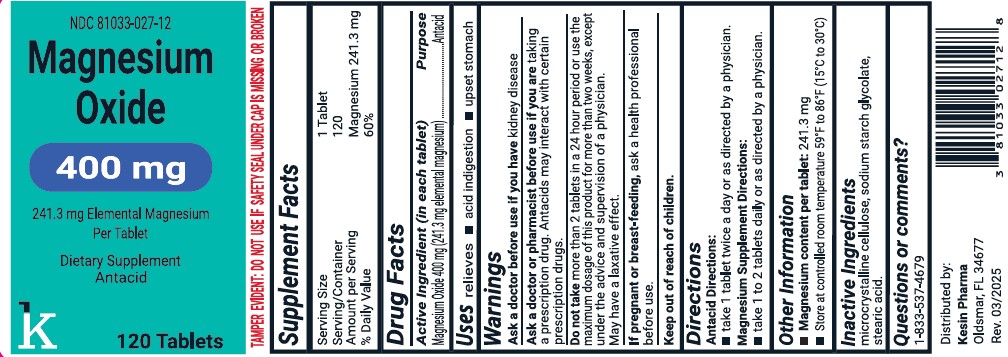 DRUG LABEL: Magnesium Oxide
NDC: 81033-027 | Form: TABLET
Manufacturer: Kesin Pharma
Category: otc | Type: HUMAN OTC DRUG LABEL
Date: 20251027

ACTIVE INGREDIENTS: MAGNESIUM OXIDE 400 mg/1 1
INACTIVE INGREDIENTS: CELLULOSE, MICROCRYSTALLINE; SODIUM STARCH GLYCOLATE TYPE A POTATO; STEARIC ACID

Magnesium Oxide Tablets 400mg

Supplement Facts

Serving Size 1 Tablet

Serving/ Container 100

Amount per Serving Magnesium 241.3 mg

% Daily Value 60%

Active Ingrendient (in each tablet)

Magnesium Oxide 400 mg (241.3 mg elemental magnesium)

Purpose

Antacid

Uses

relieves

- acid indigestion
- upset stomach

Warnings

Ask a doctor before use if you have

kidney disease

Ask a doctor or pharmacist before use if you are

taking a prescription drug. Antacids may interact with certain prescription drugs.

Do not take

more than 2 tablets in a 24 hour period or use the maximum dosage of this product for more than two weeks, except under the advice and supervision of a physician.

May have a laxative effect.

If pregnant or breast-feeding,

ask a health professional before use.

Directions

Antacid Directions:

- take 1 tablet twice a day or as directed by a physician.

Magnesium Supplement Directions:

- take 1 to 2 tablets daily or as directed by a physician.

Other Information

- Magnesium content per tablet: 241.3 mg
- Store at controlled room temperature 59ºFto 86ºF (15ºC to 30ºC)

Inactive Ingredients

microcrystalline cellulose, sodium starch glycolate, stearic acid.

Questions or comments?

1-833-537-4679

Distributed by:

Kesin Pharma

Oldsmar, FL 34677

Rev. 03/2025

PACKAGE LABEL

NDC 81033-027-12

Magnesium Oxide

400 mg

241.3 mg Elemental Magnesium

Dietary Supplement

120 Tablets

PACKAGE LABEL

NDC 81033- 027-01

Magnesium Oxide

400 mg

241.3 Elemental Magnesium per Tablet

100 Tablets (10x10 Unit-Dose)